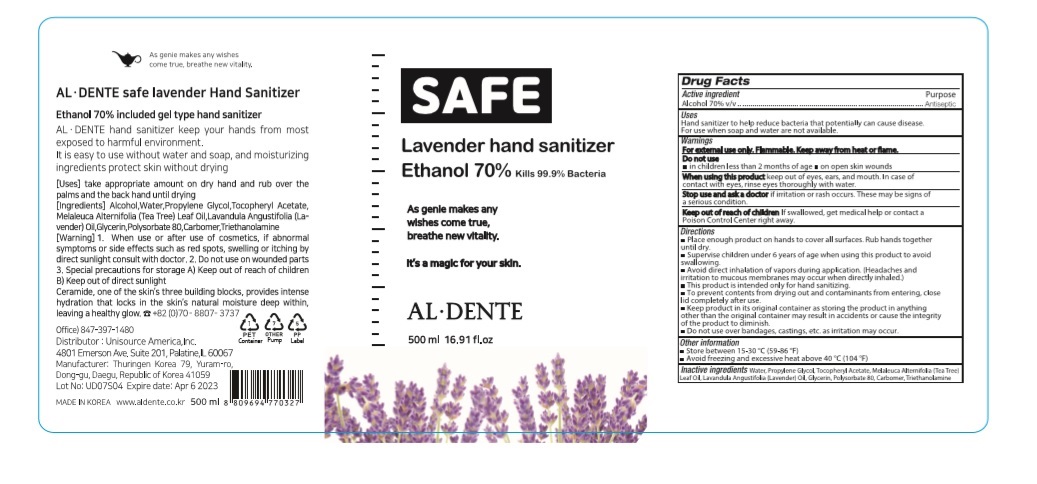 DRUG LABEL: Lavender Hand Sanitizer
NDC: 74864-0570 | Form: GEL
Manufacturer: THURINGEN KOREA Co., Ltd.
Category: otc | Type: HUMAN OTC DRUG LABEL
Date: 20200407

ACTIVE INGREDIENTS: ALCOHOL 350 mL/500 mL
INACTIVE INGREDIENTS: TEA TREE OIL; LAVENDER OIL; POLYSORBATE 80; GLYCERIN; CARBOMER HOMOPOLYMER, UNSPECIFIED TYPE; WATER; .ALPHA.-TOCOPHEROL ACETATE; PROPYLENE GLYCOL; TROLAMINE

Lavender Hand Sanitizer 500 ml : 74864-0570